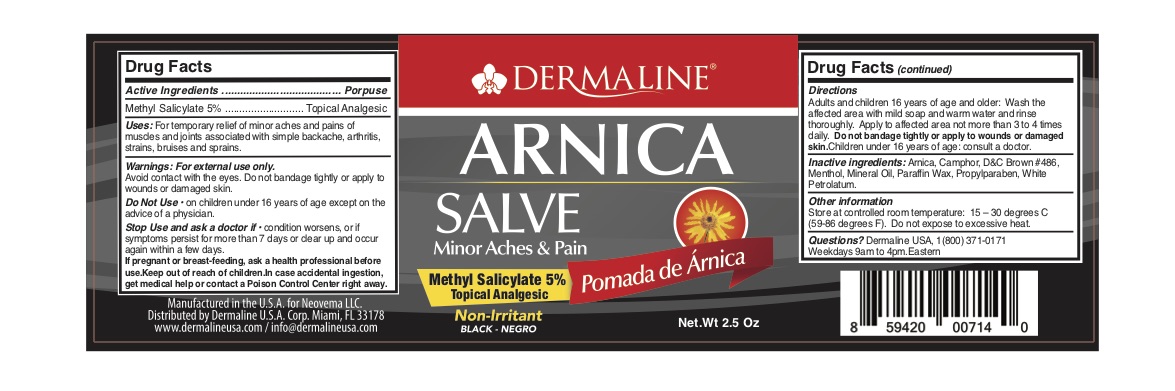 DRUG LABEL: Topical Analgesic
NDC: 82165-102 | Form: OINTMENT
Manufacturer: Dermaline USA Corp
Category: otc | Type: HUMAN OTC DRUG LABEL
Date: 20230303

ACTIVE INGREDIENTS: METHYL SALICYLATE 5 mg/100 g
INACTIVE INGREDIENTS: PARAFFIN; ARNICA MONTANA; CAMPHOR (SYNTHETIC); WHITE PETROLATUM; MENTHOL; MINERAL OIL; PROPYLPARABEN

Dermaline Arnica Salve Black

Active Ingredient(s)

Methyl Salicylate 5% Purpose: Topical Analgesic

Purpose

Topical Analgesic, Ointment

Use

For temporary relief minor aches and pains of muscles and joints associated with simple backache, arthritis, strains, bruises and sprains.

Warnings

For External Use Only. Avoid contact with the eyes. Do not bandage tightly or apply to wounds or damaged skin.

Do not Use on children under 16 years of age except on the advice of a physician.

WHEN USING

Adults and children 16 years of age and older: Wash the affected area with mild soap and warm water and rinse thoroughly. Apply to affected area not more than 3 to 4 times daily. Do not bandage tightly or apply to wounds or damaged skin. Children under 16 years of age consult a doctor.

Stop use and ask a doctor if condition worsens, or if symptoms persist for more than 7 days or clear up and occur again within a few days.

Keep out of reach of children. In case accedental ingestion, get medical help or contact a Poison Control Center right away.

Directions

Apply to affected area not more than 3 to 4 times daily.

Other information

- Store at controlled room temperature 15-30C (59-86F)
- Do not expose to excessive heat

Inactive ingredients

Arnica, Camphor, D&C Brown #486, Menthol, Mineral Oil, Paraffin Wax, Propylparaben, White Petrolatum.

Package Label - Principal Display Panel

2.5oz